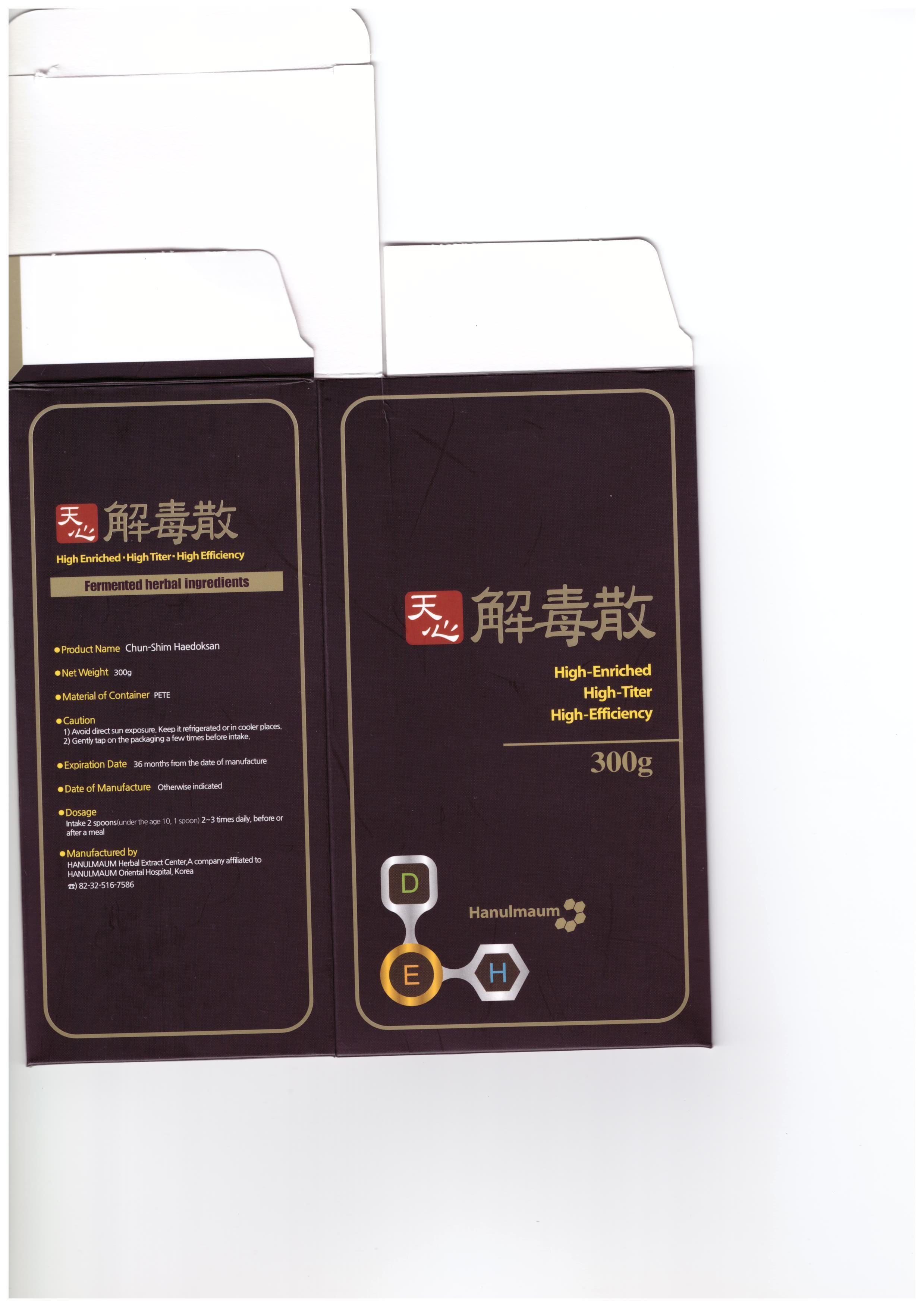 DRUG LABEL: Chun-Shim Haedoksan
NDC: 69245-1001 | Form: POWDER
Manufacturer: HAMABIO Co., Ltd.
Category: otc | Type: HUMAN OTC DRUG LABEL
Date: 20141017

ACTIVE INGREDIENTS: REHMANNIA GLUTINOSA ROOT 5 g/100 g
INACTIVE INGREDIENTS: SAPOSHNIKOVIA DIVARICATA ROOT; FU LING

Drug Facts

ACTIVE INGREDIENT

REHMANNIA GLUTINOSA ROOT

INACTIVE INGREDIENT

poris cocos, alisma canaliculatum, gypsum, anemarrhena asphodeloides, ostericum koreanum, aralia continentalis, schizonepeta tenuifolia, saposhnikovia divaricata, forsythia viridissima, lonicera japonica, arctium lappa

PURPOSE

Medicine for intractable skin disease. (e.g. Psoriasis, Atopy, Eczema, Dyshidrotic eczema, Acne, Hives, Seborrheic dermatitis, Leucoplakia, etc)

keep out or reach of the children

INDICATIONS AND USAGE

intake 2 spoons (under the age 10, spoon) 2~3 times daily before or after a meal

WARNINGS

1) avoid direct sun exposure, keep it refrigerated or in cooler places
2) gently tap on the packaging a few times before intake

DOSAGE AND ADMINISTRATION

for oral use only